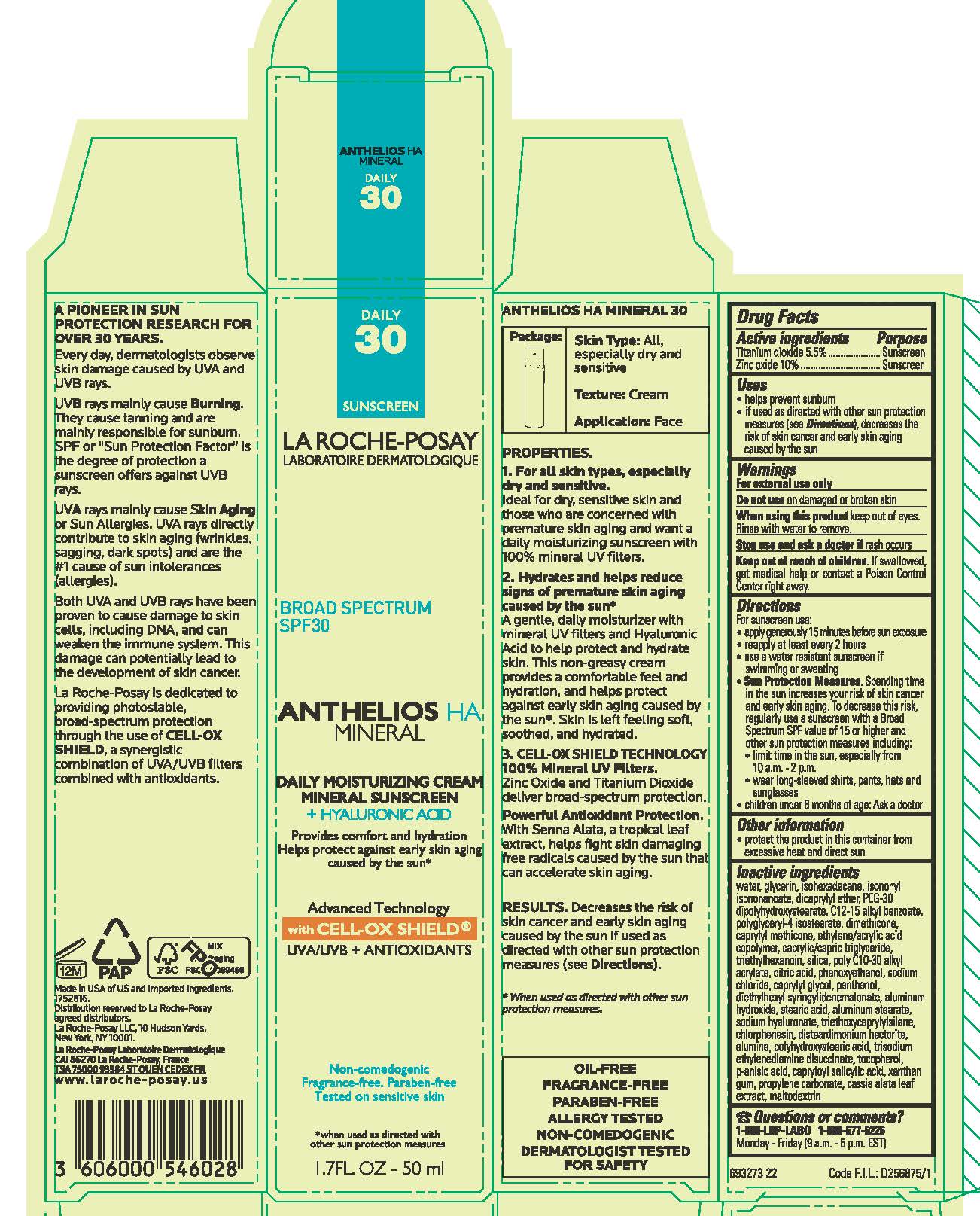 DRUG LABEL: La Roche Posay Laboratoire Dermatologique Anthelios HA Mineral Broad Spectrum SPF 30 Daily Moisturizing Sunscreen
NDC: 49967-460 | Form: CREAM
Manufacturer: L'Oreal USA Products Inc
Category: otc | Type: HUMAN OTC DRUG LABEL
Date: 20240101

ACTIVE INGREDIENTS: TITANIUM DIOXIDE 55 mg/1 mL; ZINC OXIDE 100 mg/1 mL
INACTIVE INGREDIENTS: WATER; GLYCERIN; ISOHEXADECANE; ISONONYL ISONONANOATE; DICAPRYLYL ETHER; PEG-30 DIPOLYHYDROXYSTEARATE; ALKYL (C12-15) BENZOATE; POLYGLYCERYL-4 ISOSTEARATE; DIMETHICONE; CAPRYLYL TRISILOXANE; ACRYLIC ACID/ETHYLENE COPOLYMER (600 MPA.S); MEDIUM-CHAIN TRIGLYCERIDES; TRIETHYLHEXANOIN; SILICON DIOXIDE; CITRIC ACID MONOHYDRATE; PHENOXYETHANOL; SODIUM CHLORIDE; CAPRYLYL GLYCOL; PANTHENOL; DIETHYLHEXYL SYRINGYLIDENEMALONATE; ALUMINUM HYDROXIDE; STEARIC ACID; ALUMINUM STEARATE; HYALURONATE SODIUM; TRIETHOXYCAPRYLYLSILANE; CHLORPHENESIN; DISTEARDIMONIUM HECTORITE; ALUMINUM OXIDE; POLYHYDROXYSTEARIC ACID (2300 MW); TRISODIUM ETHYLENEDIAMINE DISUCCINATE; TOCOPHEROL; P-ANISIC ACID; CAPRYLOYL SALICYLIC ACID; XANTHAN GUM; PROPYLENE CARBONATE; SENNA ALATA LEAF; MALTODEXTRIN

Drug Facts

Active ingredients

Titanium dioxide 5.5%

Zinc oxide 10%

Purpose

Sunscreen

Uses

- helps prevent sunburn

- if used as directed with other sun protection measures (see Directions), decreases the risk of skin cancer and early skin aging caused by the sun

Warnings

For external use only

Do not use

on damaged or broken skin

When using this product

keep out of eyes. Rinse with water to remove.

Stop use and ask a doctor if

rash occurs

Keep out of reach of children.

If swallowed, get medical help or contact a Poison Control Center right away.

Directions

For sunscreen use:

● apply generously 15 minutes before sun exposure

● reapply at least every 2 hours

● use a water resistant sunscreen after swimming or sweating

● immediately after towel drying

● at least every 2 hours

● Sun Protection Measures. Spending time in the sun increases your risk of skin cancer and early skin aging. To decrease this risk, regularly use a sunscreen with a Broad Spectrum SPF value of 15 or higher and other sun protection measures including:

● limit time in the sun, especially from 10 a.m. – 2 p.m.

● wear long-sleeved shirts, pants, hats, and sunglasses

● children under 6 months of age: Ask a doctor

Other information

protect the product in this container from excessive heat and direct sun

Inactive ingredients

water, glycerin, isohexadecane, isononyl isononanoate, dicaprylyl ether, PEG-30 dipolyhydroxystearate, c12-15 alkyl benzoate, polyglyceryl-4 isostearate, dimethicone, caprylyl methicone, ethylene/acrylic acid copolymer, caprylic/capric triglyceride, triethylhexanoin, silica, poly c10-30 alkyl acrylate, citric acid, phenoxyethanol, sodium chloride, caprylyl glycol, panthenol, diethylhexyl syringylidenemalonate, aluminum hydroxide, stearic acid, aluminum stearate, sodium hyaluronate, triethoxycaprylylsilane, chlorphenesin, disteardimonium hectorite, alumina, polyhydroxystearic acid, trisodium ethylenediamine disuccinate, tocopherol, p-anisic acid, capryloyl salicylic acid, xanthan gum, propylene carbonate, cassia alata leaf extract, maltodextrin

Questions or comments?

1-888-LRP-LAB0 1-888-577-5226

Monday - Friday (9 a.m. - 5 p.m. EST)